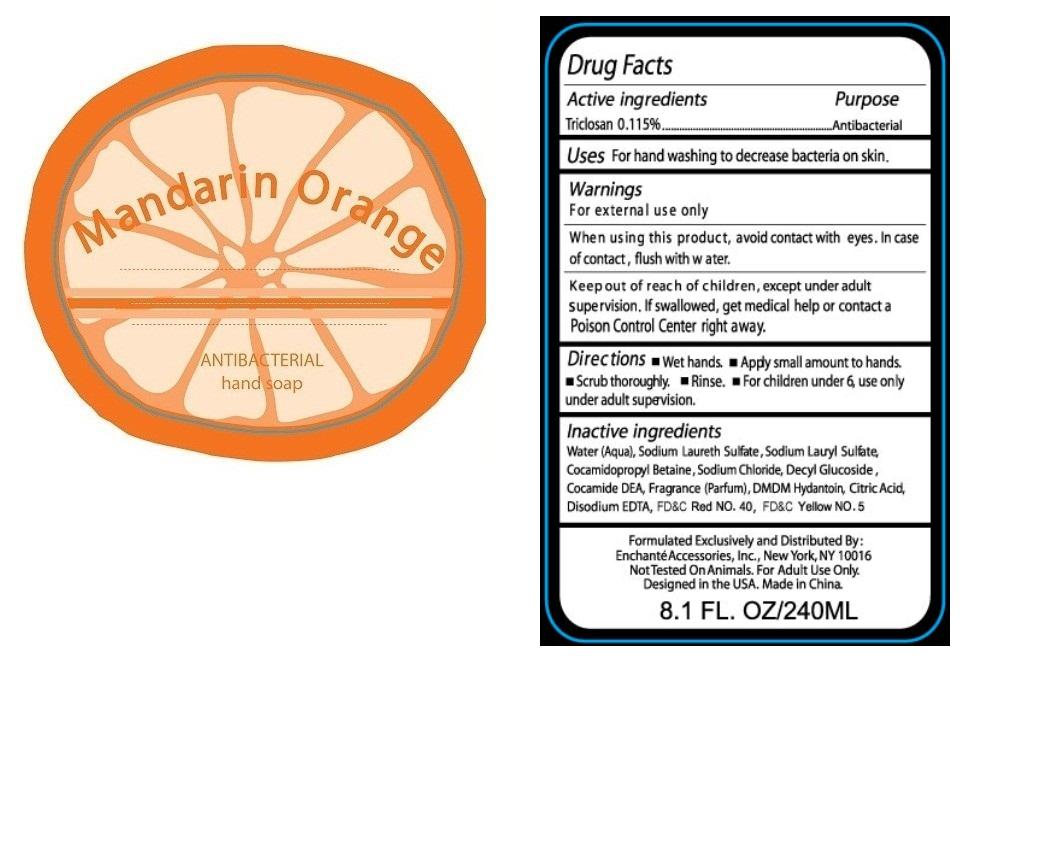 DRUG LABEL: Mandarin Orange Antibacterial Hand
NDC: 34460-6004 | Form: SOAP
Manufacturer: Zhejiang Blue Dream Cosmetics Co., Ltd.
Category: otc | Type: HUMAN OTC DRUG LABEL
Date: 20100624

ACTIVE INGREDIENTS: TRICLOSAN 0.115 g/100 g
INACTIVE INGREDIENTS: WATER 84.033 g/100 g; SODIUM LAURETH SULFATE 2.1 g/100 g; SODIUM LAURYL SULFATE 2.5 g/100 g; COCAMIDOPROPYL BETAINE 2.5 g/100 g; SODIUM CHLORIDE 2.0 g/100 g; COCAMIDE DIETHANOLAMINE 1.5 g/100 g; DMDM HYDANTOIN 1.3 g/100 g; ANHYDROUS CITRIC ACID 1.1 g/100 g; EDETATE DISODIUM 1.25 g/100 g; FD&C RED NO. 40 0.001 g/100 g; ORANGE 0.3 g/100 g; FD&C YELLOW NO. 5 0.001 g/100 g

DRUG FACT

Active Ingredient Purpose

Triclosan 0.115% Antibacteria

INDICATIONS AND USAGE

Uses: For hand washing to decrease bacteria on skin

Warnings:

For external use only

When using this product, avoid contact with eyes. In case of contact, flush with water

Keep out of reach of children, except under adult supervision. If swallowed, get medical help or contact a Poison Control Center right away.

Directions:

- Wet hands
- Apply small amount to hands
- Scrub thoroughly
- Rinse
- For children under 6, use only under adult supervision.

Inactive Ingredient:

Water (aqua), Sodium Laureth Sulfate, Sodium Lauryl Sulfate, Cocamidopropyl Betaine, Sodium Chloride, Decyl Glucoside, Cocamide DEA, Fragrance (Parfum), DMDM Hydantoin, Citric Acid, Disodium EDTA, FD and C Red No. 40, FD and C Yellow No. 5

PACKAGE LABEL

pictu